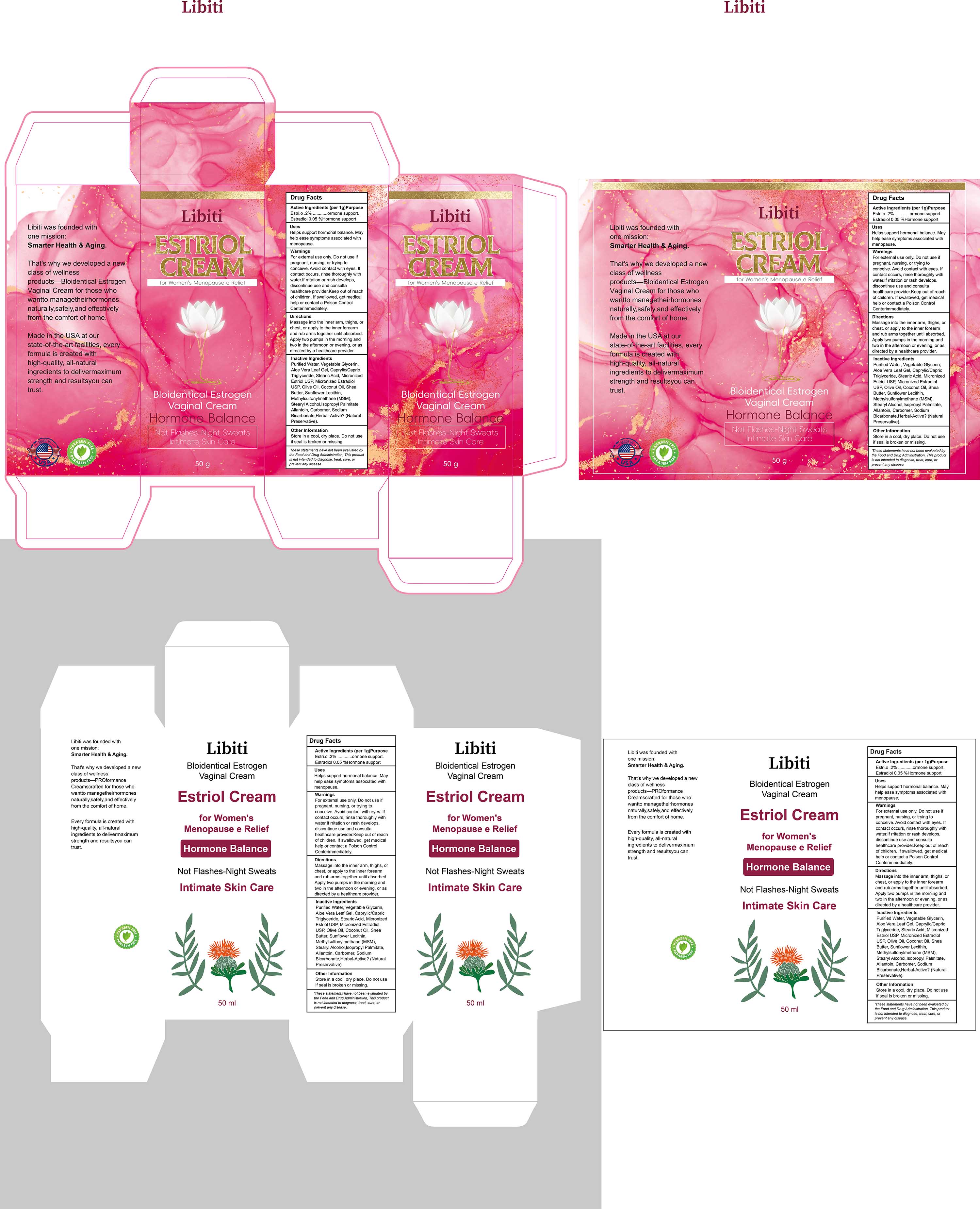 DRUG LABEL: Estriol cream
NDC: 84735-014 | Form: CREAM
Manufacturer: Hengyang Chuangjiujia Trading Co., Ltd.
Category: otc | Type: HUMAN OTC DRUG LABEL
Date: 20251112

ACTIVE INGREDIENTS: ESTRADIOL 0.02 g/100 g; ESTRIOL 2 g/100 g
INACTIVE INGREDIENTS: LECITHIN, SUNFLOWER; SHEA BUTTER; CARBOMER; COCONUT OIL; DIMETHYL SULFONE; ALLANTOIN; GLYCERIN; OLIVE OIL; ALOE VERA LEAF; ISOPROPYL PALMITATE; STEARYL ALCOHOL; SODIUM BENZOATE; WATER; POTASSIUM SORBATE; CAPRYLIC/CAPRIC TRIGLYCERIDE; STEARIC ACID

84735-014 Estriol cream

ACTIVE INGREDIENT

Estriol
Estradiol

PURPOSE

Hormone support

INDICATIONS AND USAGE

Helps support hormonal balance. Mayhelp ease symptoms associated with menopause

WARNINGS

For external use only.

Do not use ifpregnant, nursing, or trying toconceive.

WHEN USING

Avoid contact with eyes.lfcontact occurs, rinse thoroughly withwater.
lf rritation or rash develops,discontinue use and consultahealthcare provider.

Keep out of reachof children.
lf swallowed, get medicalhelp or contact a Poison Control Centerimmediately

DOSAGE AND ADMINISTRATION

Massage into the inner arm, thighs, orchest, or apply to the inner forearmand rub arms together until absorbedApply two pumps in the morning andtwo in the afternoon or evening, or asdirected by a healthcare provider.

INACTIVE INGREDIENT

Purified Water
Vegetable Glycerin
Aloe Vera Leaf Gel
Caprylic/Capric Triglyceride
Stearic Acid
Olive Oil
Coconut Oil
Shea Butter
Sunflower Lecithin
Methylsulfonylmethane (MSM)
Stearyl Alcohol
Isopropyl Palmitate
Allantoin
Carbomer
Sodium Benzoate
Potassium Sorbate